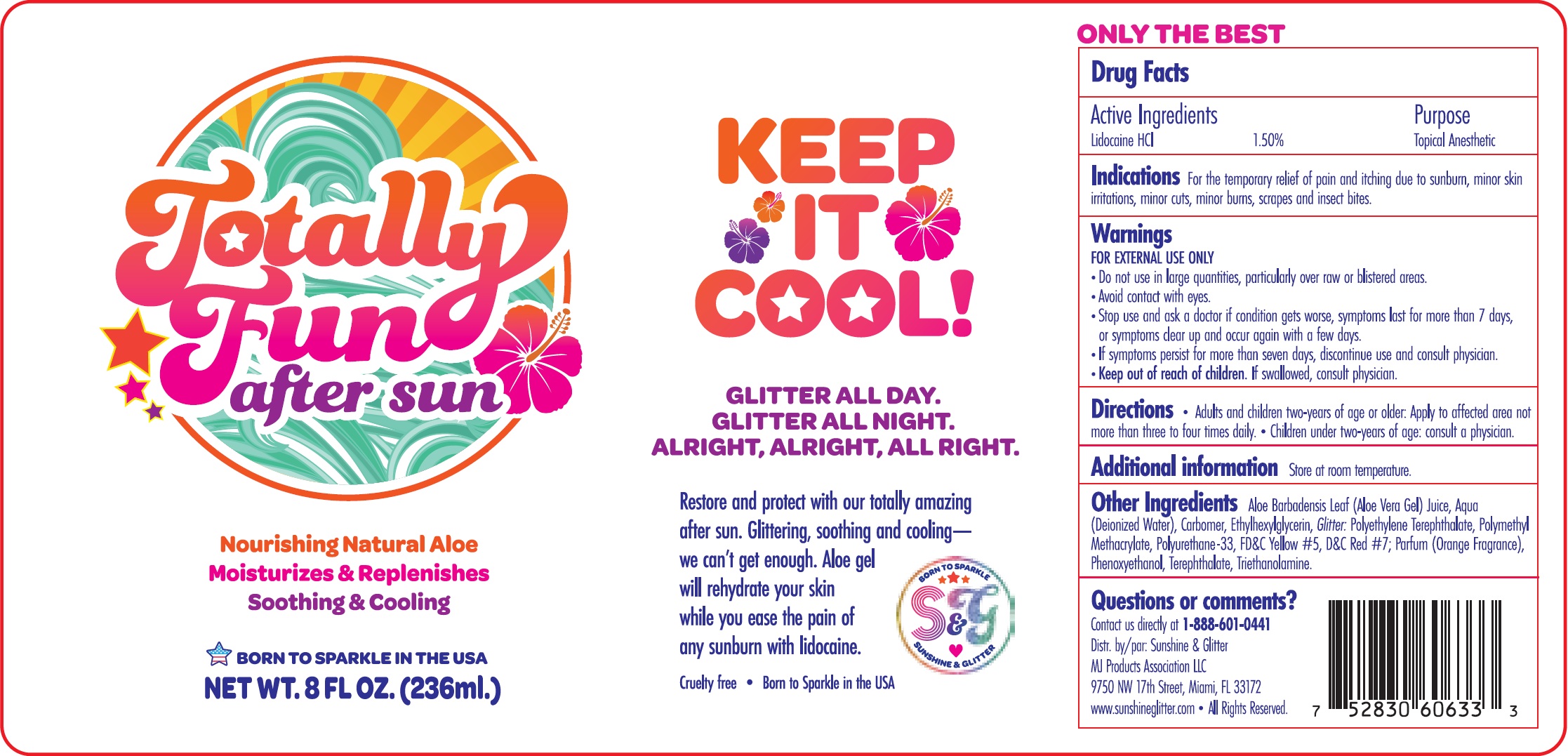 DRUG LABEL: Totally Fun After Sun
NDC: 72085-145 | Form: GEL
Manufacturer: MJ Products Association, LLC
Category: otc | Type: HUMAN OTC DRUG LABEL
Date: 20231115

ACTIVE INGREDIENTS: LIDOCAINE HYDROCHLORIDE 15 mg/1 mL
INACTIVE INGREDIENTS: ALOE VERA LEAF; WATER; CARBOXYPOLYMETHYLENE; ETHYLHEXYLGLYCERIN; POLY(METHYL METHACRYLATE; 450000 MW); FD&C YELLOW NO. 5; D&C RED NO. 7; PHENOXYETHANOL; TROLAMINE

Totally Fun After Sun

Active Ingredients

Lidocaine HCL 1.50%

PURPOSE

Topical Anesthetic

Indications

For the Temporary relief of pain and itching due to sunburn, minor skin irritations, minor cuts, minor burns, scrapes and insect bites.

WARNINGS

FOR EXTERNAL USE ONLY

Do not use

- in large quantites, particularly over raw or blistered areas.
- Avoid contact with eyes.

Stop use and ask a doctor

- if condition gets worse, symptoms last for more than 7 days, or symptoms clear up and occur again with a few days.
- If sumptoms persist for more than seven days, discontinue use and consult physician.

Keep out of reach of children.

If swallowed, consult physician.

Directions

- Adults and children two-years of age or older: Apply to affected area not more than three to four times daily.
- Children under two-years of age: consult a physician.

Additional information

Store at room temperature.

Other Ingredients

Aloe Barbadensis Leaf (Aloe Vera Gel) Juice, Aqua (Deionized Water), Carbomer, Ethylhexylglycerin, : Polyethylene Terephthalate, Polymethyl Methacrylate, Polyurethan-33, FD&C Yellow #5, D&C Red #7; Parfum (Orange Fragrance), Phenoxyethanol, Terephthalate, Triethanolamine. Glitter

Questions or comments?

Contact us directly at 1-888-601-0441

Distr. by/par: Sunshine & Glitter

MJ Products Association LLC

9750 NW 17th Street, Miami, FL 33172

www.sunshineglitter.com

All Rights Reserved.